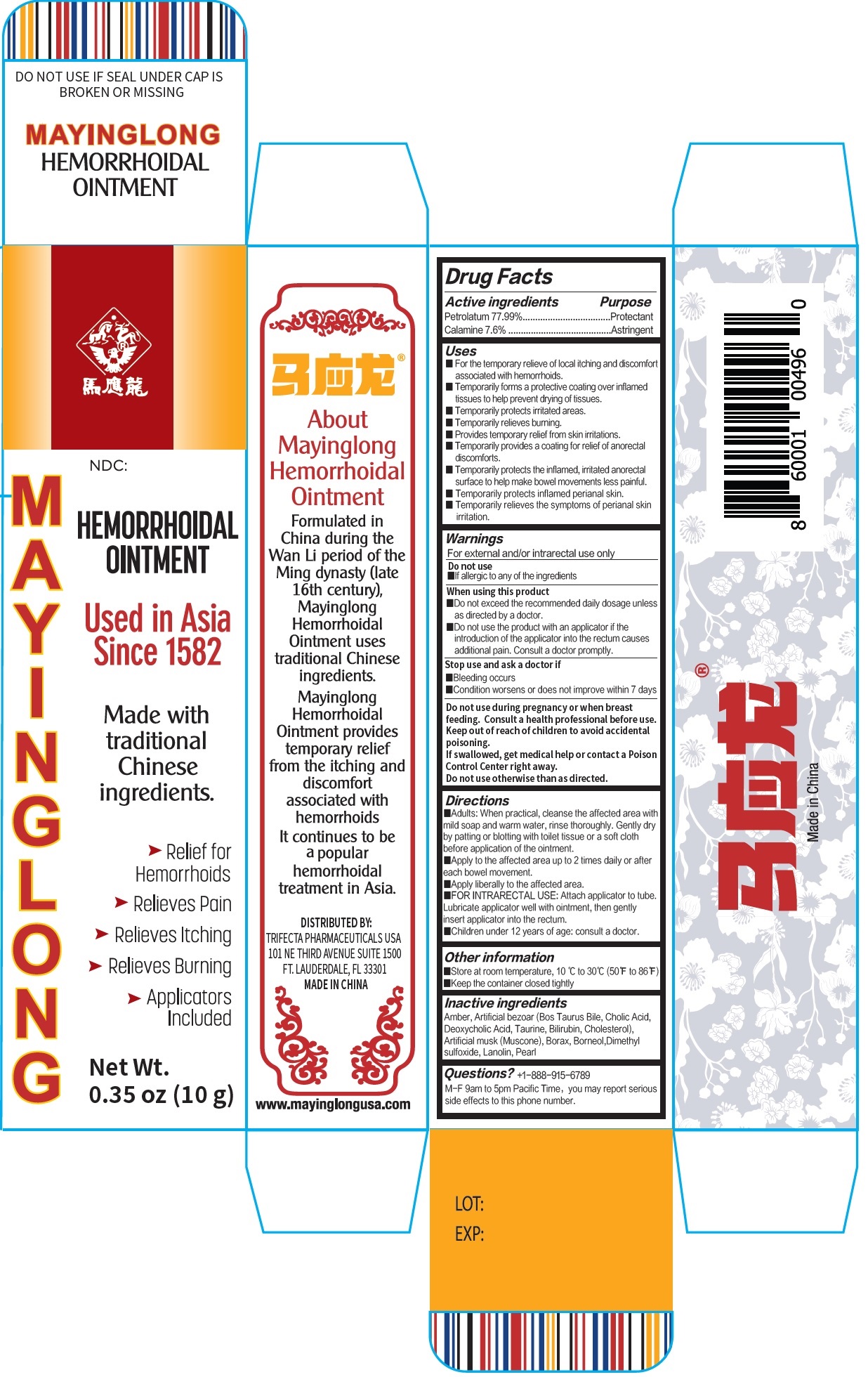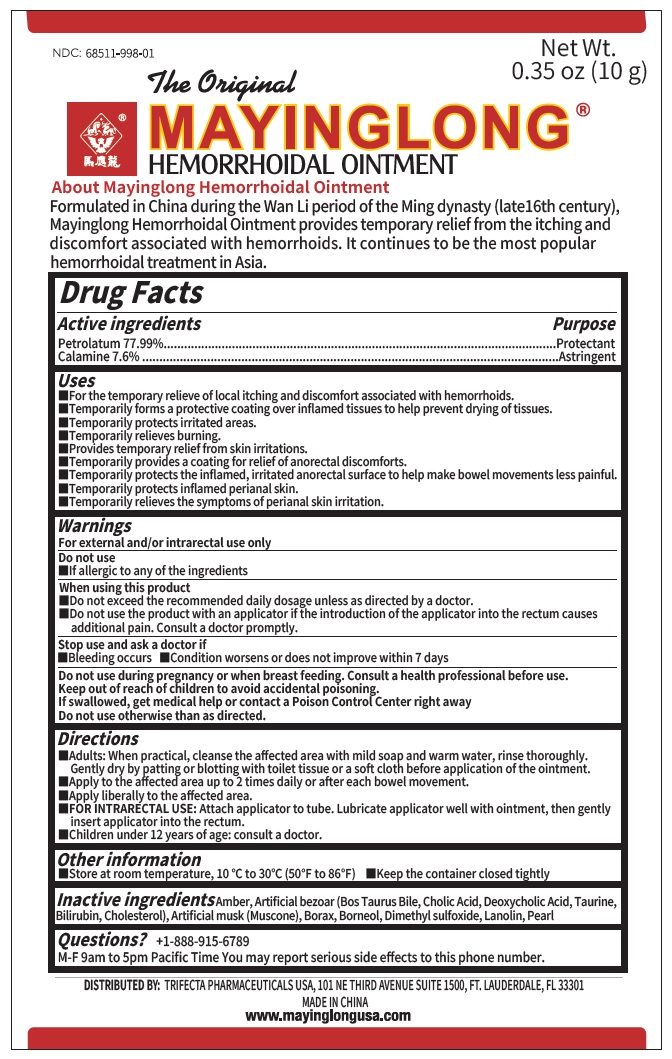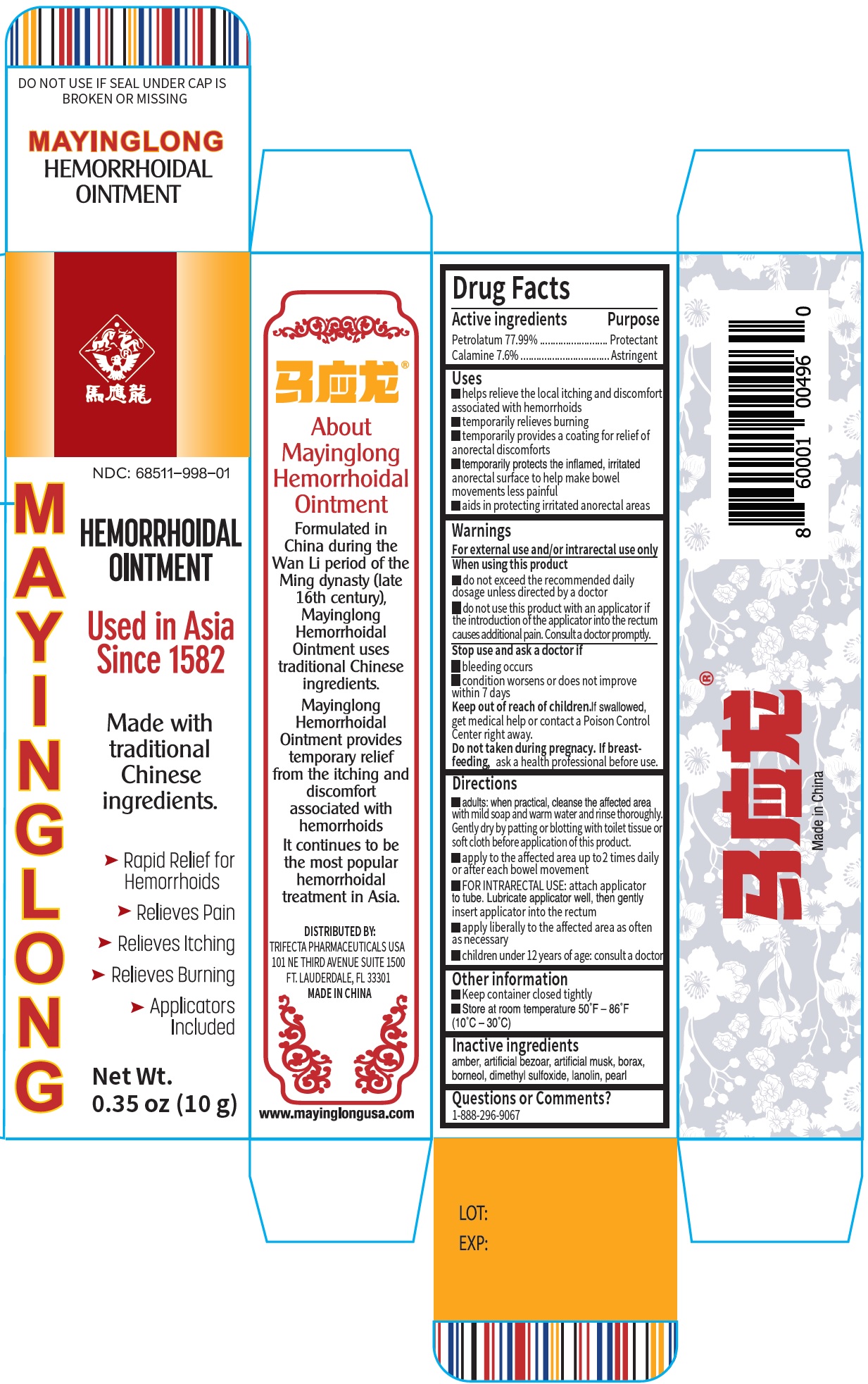 DRUG LABEL: Mayinglong Hemorrhoidal
NDC: 68511-998 | Form: OINTMENT
Manufacturer: Mayinglong Pharmaceutical Group Co., Ltd.
Category: otc | Type: HUMAN OTC DRUG LABEL
Date: 20231208

ACTIVE INGREDIENTS: PETROLATUM 779.9 mg/1 g; ZINC OXIDE 76 mg/1 g
INACTIVE INGREDIENTS: AMBER; BOS TAURUS BILE; CHOLIC ACID; DEOXYCHOLIC ACID; TAURINE; BILIRUBIN; CHOLESTEROL; MUSCONE; SODIUM BORATE; BORNEOL; DIMETHYL SULFOXIDE; LANOLIN; PEARL (HYRIOPSIS CUMINGII)

Mayinglong Hemorrhoidal Ointment

Active ingredients

Petrolatum 77.99%

Calamine 7.6%

Purpose

Protectant

Astringent

Uses

- For the temporary relieve of local itching and discomfort associated with hemorrhoids.
- Temporarily forms a protective coating over inflamed tissues to help prevent drying of tissues.
- Temporarily protects irritated areas.
- Temporarily relieves burning.
- Provides temporary relief from skin irritations.
- Temporarily provides a coating for relief of anorectal discomforts.
- Temporarily protects the inflamed, irritated anorectal surface to help make bowel movements less painful.
- Temporarily protects inflamed perianal skin.
- Temporarily relieves the symptoms of perianal skin irritation.

Warnings

For external use and/or intrarectal use only

Do not use

- If allergic to any of the ingredients

When using this product

- Do not exceed the recommended daily dosage unless as directed by a doctor.
- Do not use the product with an applicator if the introduction of the applicator into the rectum causes additional pain. Consult a doctor promptly.

Stop use and ask a doctor if

- Bleeding occurs
- Condition worsens or does not improve within 7 days

Do not use during pregnancy or when breast feeding.

Consult a health professional before use.

Keep out of reach of children

to avoid accidental poisoning. If swallowed, get medical help or contact a Poison Control Center right away Do not use otherwise than as directed.

Directions

- Adults: When practical, cleanse the affected area with mild soap and warm water, rinse thoroughly. Gently dry by patting or blotting with toilet tissue or a soft cloth before application of the ointment.

- Apply to the affected area up to 2 times daily or after each bowel movement.
- Apply liberally to the affected area.
- Attach applicator to tube. Lubricate applicator well with ointment, then gently insert applicator into the rectum. FOR INTRARECTAL USE:

- Children under 12 years of age: consult a doctor.

Other information

- Store at room temperature, 10 ℃ to 30℃ (50℉ to 86℉)
- Keep the container closed tightly

Inactive ingredients

Amber, Artificial bezoar (Bos Taurus Bile, Cholic Acid,D eoxycholic Acid, Taurine, Bilirubin, Cholesterol), Artificial musk (Muscone), Borax, Borneol, Dimethyl sulfoxide, Lanolin, Pear

Questions?

+1-888-915-6789 M-F 9am to 5pm Pacific Time You may report serious side effects to this phone number.